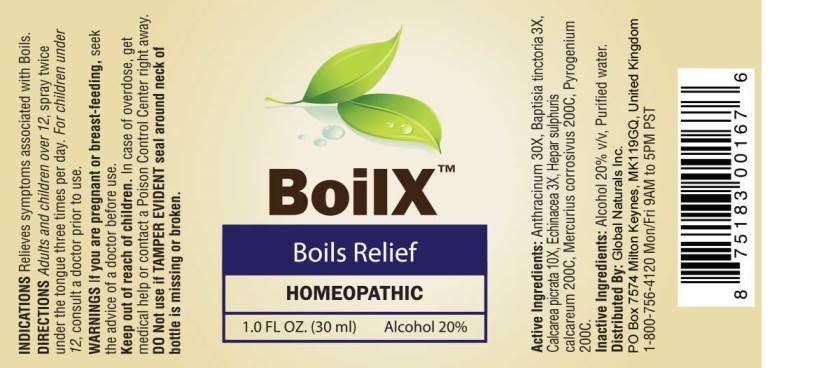 DRUG LABEL: BoilX
NDC: 43695-0012 | Form: SPRAY
Manufacturer: Global Naturals, Inc.
Category: homeopathic | Type: HUMAN OTC DRUG LABEL
Date: 20180601

ACTIVE INGREDIENTS: BACILLUS ANTHRACIS IMMUNOSERUM RABBIT 30 [hp_X]/1 mL; BAPTISIA TINCTORIA ROOT 3 [hp_X]/1 mL; CALCIUM PICRATE 10 [hp_X]/1 mL; ECHINACEA ANGUSTIFOLIA 3 [hp_X]/1 mL; CALCIUM SULFIDE 200 [hp_C]/1 mL; MERCURIC CHLORIDE 200 [hp_C]/1 mL; RANCID BEEF 200 [hp_C]/1 mL
INACTIVE INGREDIENTS: WATER; ALCOHOL

Drug Facts:

ACTIVE INGREDIENTS:

Anthracinum 30X, Baptisia Tinctoria 3X, Calcarea Picrata 10X, Echinacea (Angustifolia) 3X, Hepar Sulphuris Calcareum 200C, Mercurius Corrosivus 200C, Pyrogenium 200C.

INDICATIONS:

Relieves symptoms associated with Boils.

WARNINGS:

If you are pregnant or breast-feeding, seek the advice of a doctor before use.

Keep out of reach of children. In case of overdose, get medical help or contact a Poison Control Center right away.

DO Not use if TAMPER EVIDENT seal around neck of bottle is missing or broken.

Keep out of reach of children. In case of overdose, get medical help or contact a Poison Control Center right away.

DIRECTIONS:

Adults and children over 12, spray twice under the tongue three times per day. For children under 12, consult a doctor prior to use.

INDICATIONS:

Relieves symptoms associated with Boils.

INACTIVE INGREDIENTS:

Alcohol 20% v/v, Purified water.

QUESTIONS:

Distributed By: Global Naturals Inc.
PO Box 7574 Milton Keynes, MK119GQ, United Kingdom
1-800-756-4120 Mon/Fri 9AM to 5PM PST

PACKAGE LABEL DISPLAY:

BoilX

Boils Relief

HOMEOPATHIC

1.0 FL oz. (30 ml)